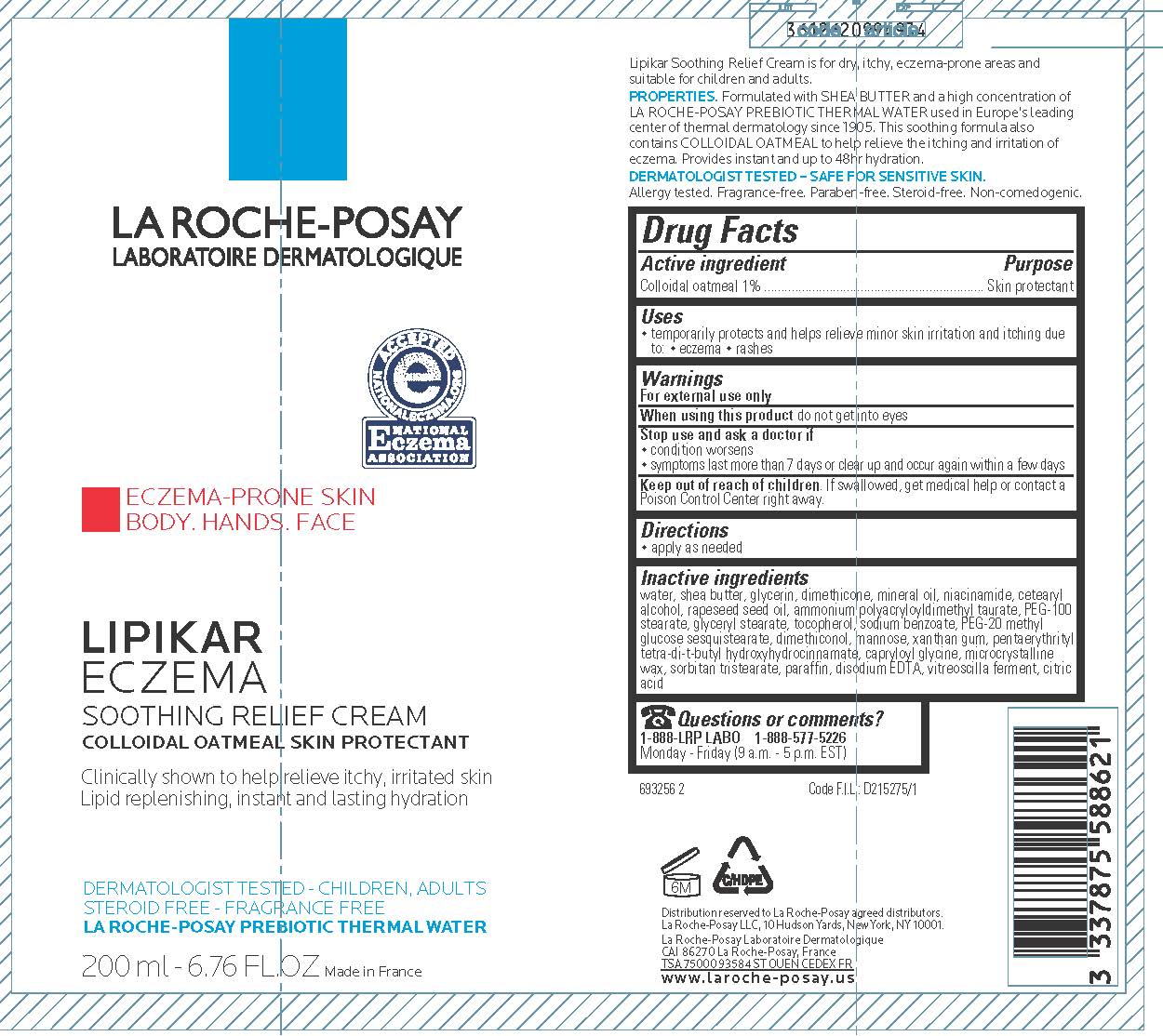 DRUG LABEL: La Roche Posay Laboratoire Dermatologique Lipikar Eczema Relief
NDC: 69625-620 | Form: CREAM
Manufacturer: COSMETIQUE ACTIVE PRODUCTION
Category: otc | Type: HUMAN OTC DRUG LABEL
Date: 20231211

ACTIVE INGREDIENTS: OATMEAL 10 mg/1 mL
INACTIVE INGREDIENTS: WATER; SHEA BUTTER; GLYCERIN; DIMETHICONE; MINERAL OIL; NIACINAMIDE; CETOSTEARYL ALCOHOL; CANOLA OIL; PEG-100 STEARATE; GLYCERYL MONOSTEARATE; TOCOPHEROL; SODIUM BENZOATE; PEG-20 METHYL GLUCOSE SESQUISTEARATE; DIMETHICONOL (100000 CST); MANNOSE, D-; XANTHAN GUM; PENTAERYTHRITOL TETRAKIS(3-(3,5-DI-TERT-BUTYL-4-HYDROXYPHENYL)PROPIONATE); CAPRYLOYL GLYCINE; MICROCRYSTALLINE WAX; SORBITAN TRISTEARATE; PARAFFIN; EDETATE DISODIUM; CITRIC ACID MONOHYDRATE

Drug Facts

Active ingredient

Colloidal oatmeal 1%

Purpose

Skin protectant

Uses

- temporarily protects and helps relieve minor skin irritation and itching due to: •eczema •rashes

Warnings

For external use only

When using this product

do not get into eyes

Stop use and ask a doctor if

- condition worsens
- symptoms last more than 7 days or clear up and occur again within a few days

Keep out of reach of children.

If swallowed, get medical help or contact a Poison Control Center right away.

Directions

apply as needed

Inactive ingredients

water, shea butter, glycerin, dimethicone, mineral oil, niacinamide, cetearyl alcohol, rapeseed seed oil, ammonium polyacryloyldimethyl taurate, PEG-100 stearate, glyceryl stearate, tocopherol, sodium benzoate, PEG-20 methyl glucose sesquistearate, dimethiconol, mannose, xanthan gum, pentaerythrityl tetra-di-t-butyl hydroxyhydrocinnamate, capryloyl glycine, microcrystalline wax, sorbitan tristearate, paraffin, discodium EDTA, vitreoscilla ferment, citric acid

Questions or comments?

1-888-LRP LABO

1-888-577-5226

Monday - Friday (9 a.m. - 5 p.m. EST)